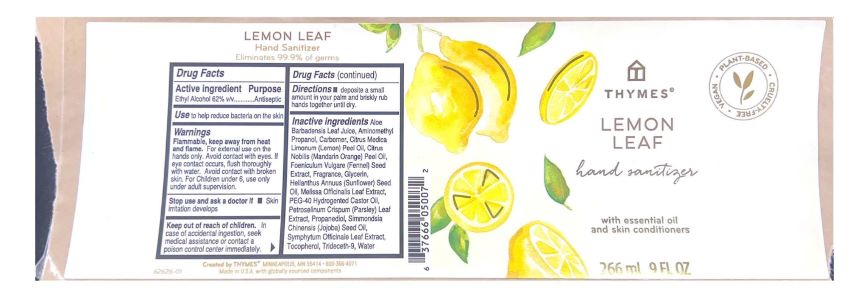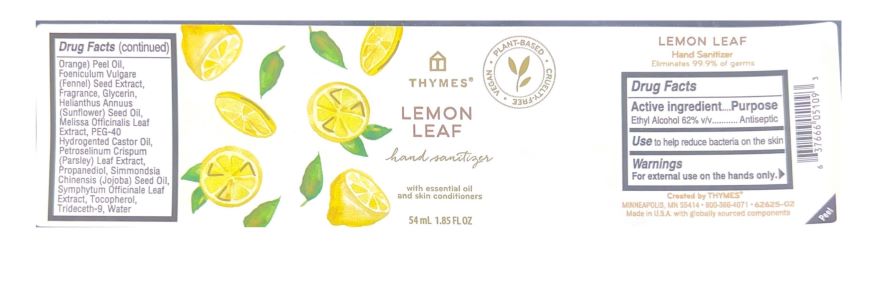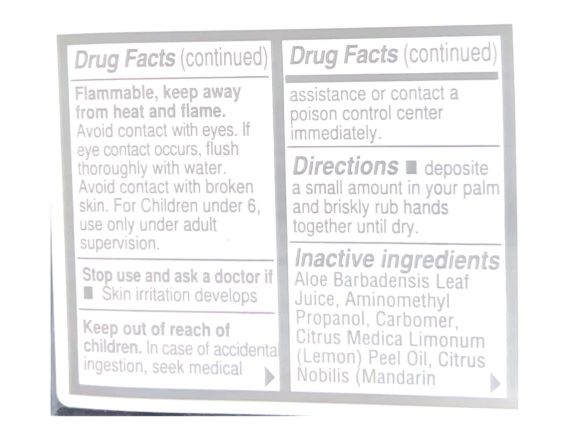 DRUG LABEL: Thymes Lemon Leaf Hand Sanitizer
NDC: 76150-338 | Form: GEL
Manufacturer: Bell International Laboratories, Inc
Category: otc | Type: HUMAN OTC DRUG LABEL
Date: 20220407

ACTIVE INGREDIENTS: ALCOHOL 62 mL/100 mL
INACTIVE INGREDIENTS: FENNEL SEED; TOCOPHEROL; WATER; AMINOMETHYLPROPANOL; GLYCERIN; ALOE VERA LEAF; JOJOBA OIL; COMFREY LEAF; TRIDECETH-9; PROPANEDIOL; SUNFLOWER OIL; POLYOXYL 40 HYDROGENATED CASTOR OIL; PARSLEY; MELISSA OFFICINALIS LEAF; CARBOMER HOMOPOLYMER, UNSPECIFIED TYPE; LEMON OIL, COLD PRESSED; MANDARIN OIL

Thymes Lemon Leaf Hand Sanitizer

Active Ingredient

Ethyl Alcohol 62% v/v

Purpose

Antiseptic

Use

To help reduce bacteria on the skin

Warnings

Flammable, keep away from heat and flame. For external use on the hands only. Avoid contact with eyes. If eye contact occurs, flush thoroughly with water. Avoid contact with broken skin. For Children under 6, use only under adult supervision.

Stop use and ask a doctor if skin irritation develops

Keep out of reach of children. In case of accidental ingestion, seek medical assistance or contact a poison control center immediately.

Directions

Deposit a small amount in your palm and briskly rub hands together until dry.

Inactive Ingredients

Aloe Barbadensis Leaf Juice, Aminomethyl Propanol, Carbomer, Citrus Medica Limonum (Lemon) Peel Oil, Citrus Nobilis (Mandarin Orange) Peel Oil, Foeniculum Vulgare (Fennel) Seed Extract, Fragrance, Glycerin, Helianthus Annuus (Sunflower) Seed Oil, Melissa Officinalis Leaf Extract, PEG-40 Hydrogenated Castor Oil, Petroselinum Crispum (Parsley) Leaf Extract, Propanediol, Simmondsia Chinensis (Jojoba) Seed Oil, Symphytum Officinale Leaf Extract, Tocopherol, Trideceth-9, Water